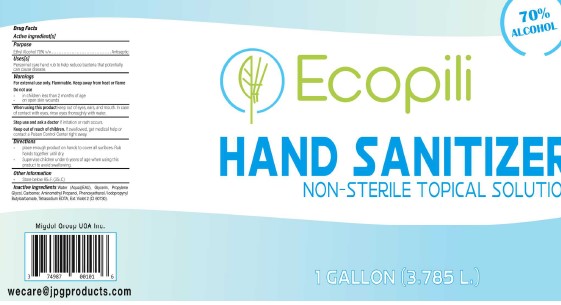 DRUG LABEL: Hand Sanitizer
NDC: 74987-001 | Form: LIQUID
Manufacturer: Migdol Group Usa, Inc.
Category: otc | Type: HUMAN OTC DRUG LABEL
Date: 20200723

ACTIVE INGREDIENTS: ALCOHOL 70 mL/100 mL
INACTIVE INGREDIENTS: PROPYLENE GLYCOL; AMINOMETHYLPROPANOL; PHENOXYETHANOL; IODOPROPYNYL BUTYLCARBAMATE; EDETATE SODIUM; EXT. D&C VIOLET NO. 2; CARBOMER 940; GLYCERIN; WATER

Ecopilli 74987-001

Active Ingredient(s)

Alcohol 70% v/v. Purpose: Antiseptic

Purpose

Antiseptic, Hand Sanitizer

Use

Hand Sanitizer to help reduce bacteria that potentially can cause disease. For use when soap and water are not available.

Warnings

For external use only. Flammable. Keep away from heat or flame

Do not use

- in children less than 2 months of age
- on open skin wounds

When using this product keep out of eyes, ears, and mouth. In case of contact with eyes, rinse eyes thoroughly with water.

Stop use and ask a doctor if irritation or rash occurs. These may be signs of a serious condition.

Keep out of reach of children. If swallowed, get medical help or contact a Poison Control Center right away.

Directions

- Place enough product on hands to cover all surfaces. Rub hands together until dry.
- Supervise children under 6 years of age when using this product to avoid swallowing.

Other information

- Store below 95F (35C)

Inactive ingredients

water, glycerin, propylene glycol, carbomer, aminomethyl propanol, phenoxyethanol, iodopropynyl butylcarbamate, tetrasodium EDTA, Ext. Violet 2.

Package Label - Principal Display Panel

3785 mL NDC: 74987-001-01